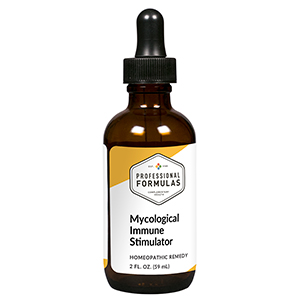 DRUG LABEL: Mycological Immune Stimulator
NDC: 63083-6010 | Form: LIQUID
Manufacturer: Professional Complementary Health Formulas
Category: homeopathic | Type: HUMAN OTC DRUG LABEL
Date: 20190815

ACTIVE INGREDIENTS: SODIUM BORATE 6 [hp_X]/59 mL; LACTIC ACID, DL- 6 [hp_X]/59 mL; BOS TAURUS LYMPH VESSEL 6 [hp_X]/59 mL; HANDROANTHUS IMPETIGINOSUS BARK 6 [hp_X]/59 mL; BOS TAURUS SPLEEN 6 [hp_X]/59 mL; HYSSOPUS OFFICINALIS WHOLE 6 [hp_X]/59 mL; PLEOSPORA HERBARUM 30 [hp_X]/59 mL; ASPERGILLUS FLAVUS 30 [hp_X]/59 mL; ASPERGILLUS FUMIGATUS 30 [hp_X]/59 mL; EUROTIUM HERBARIORUM 30 [hp_X]/59 mL; ASPERGILLUS NIDULANS 30 [hp_X]/59 mL; ASPERGILLUS NIGER VAR. NIGER 30 [hp_X]/59 mL; BLASTOCYSTIS HOMINIS 30 [hp_X]/59 mL; CANDIDA ALBICANS 30 [hp_X]/59 mL; CANDIDA PARAPSILOSIS 30 [hp_X]/59 mL; CANDIDA TROPICALIS 30 [hp_X]/59 mL; CLADOSPORIUM SPHAEROSPERMUM 30 [hp_X]/59 mL; COLCHICUM AUTUMNALE BULB 30 [hp_X]/59 mL; RHODOTORULA RUBRA 30 [hp_X]/59 mL; COCHLIOBOLUS SPICIFER 30 [hp_X]/59 mL; TRICHOPHYTON RUBRUM 30 [hp_X]/59 mL; SACCHAROMYCES CEREVISIAE 30 [hp_X]/59 mL; GIBBERELLA FUJIKUROI 30 [hp_X]/59 mL; GEOTRICHUM CANDIDUM 30 [hp_X]/59 mL; MUCOR PLUMBEUS 30 [hp_X]/59 mL; MUCOR RACEMOSUS 30 [hp_X]/59 mL; PENICILLIN G 30 [hp_X]/59 mL; AUREOBASIDIUM PULLULANS VAR. PULLUTANS 30 [hp_X]/59 mL; RHIZOPUS STOLONIFER 30 [hp_X]/59 mL; TRICHOPHYTON TONSURANS 30 [hp_X]/59 mL
INACTIVE INGREDIENTS: ALCOHOL; WATER

X10

ACTIVE INGREDIENTS

Borax 6X
L+ Lactic acid 6X
Lymph 6X
Pau D'Arco 6X
Spleen 6X
Thymus 6X
and all the following at 30X, 60X:
Alternaria
Aspergillus flavus
Aspergillus fumigatus
Aspergillus glaucus
Aspergillus nidulans
Aspergillus niger
Blastomyces
Candida albicans
Candida parapsilosis
Candida rugosa
Candida tropicalis
Cladosporium sphaerospermum
Colchicum autumnale
Cryptococcus sp.
Curvularia spicifera
Epidermophyton sp.
Faex medicinalis
Fusarium moniliforme
Geotrichum sp.
Mucor plumbeus
Mucor racemosus
Mycosis fungoides
Penicillium G
Pullularia pullulans
Rhizopus nigricans
Trichophyton sp.
Trichosporon sp.

QUESTIONS

Professional Formulas

PO Box 2034 Lake Oswego, OR 97035

INDICATIONS

For the temporary relief of runny nose, sneezing, itching of the nose or throat, itchy or watery eyes, cough, shortness of breath, occasional headache, red or itchy skin, irritability, or fatigue.*

PURPOSE

*Claims based on traditional homeopathic practice, not accepted medical evidence. Not FDA evaluated.

WARNINGS

Persistent symptoms may be a sign of a serious condition. If symptoms persist or are accompanied by a fever, rash, or persistent headache, consult a doctor. Keep out of the reach of children. In case of overdose, get medical help or contact a poison control center right away. If pregnant or breastfeeding, ask a healthcare professional before use.

Keep out of the reach of children.

PREGNANCY OR BREAST FEEDING

If pregnant or breastfeeding, ask a healthcare professional before use.

DIRECTIONS

Place drops under tongue 30 minutes before/after meals. Adults and children 12 years and over: Take 10 drops up to 3 times per day. Consult a physician for use in children under 12 years of age.

OTHER INFORMATION

Tamper resistant. If seal is broken, do not use. After opening, close container tightly and store at room temperature away from heat.

INACTIVE INGREDIENTS

20% ethanol, purified water.

LABEL

Est 1985

Professional Formulas

Complementary Health

Mycological Immune Stimulator

Homeopathic Remedy

2 FL. OZ. (59 mL)